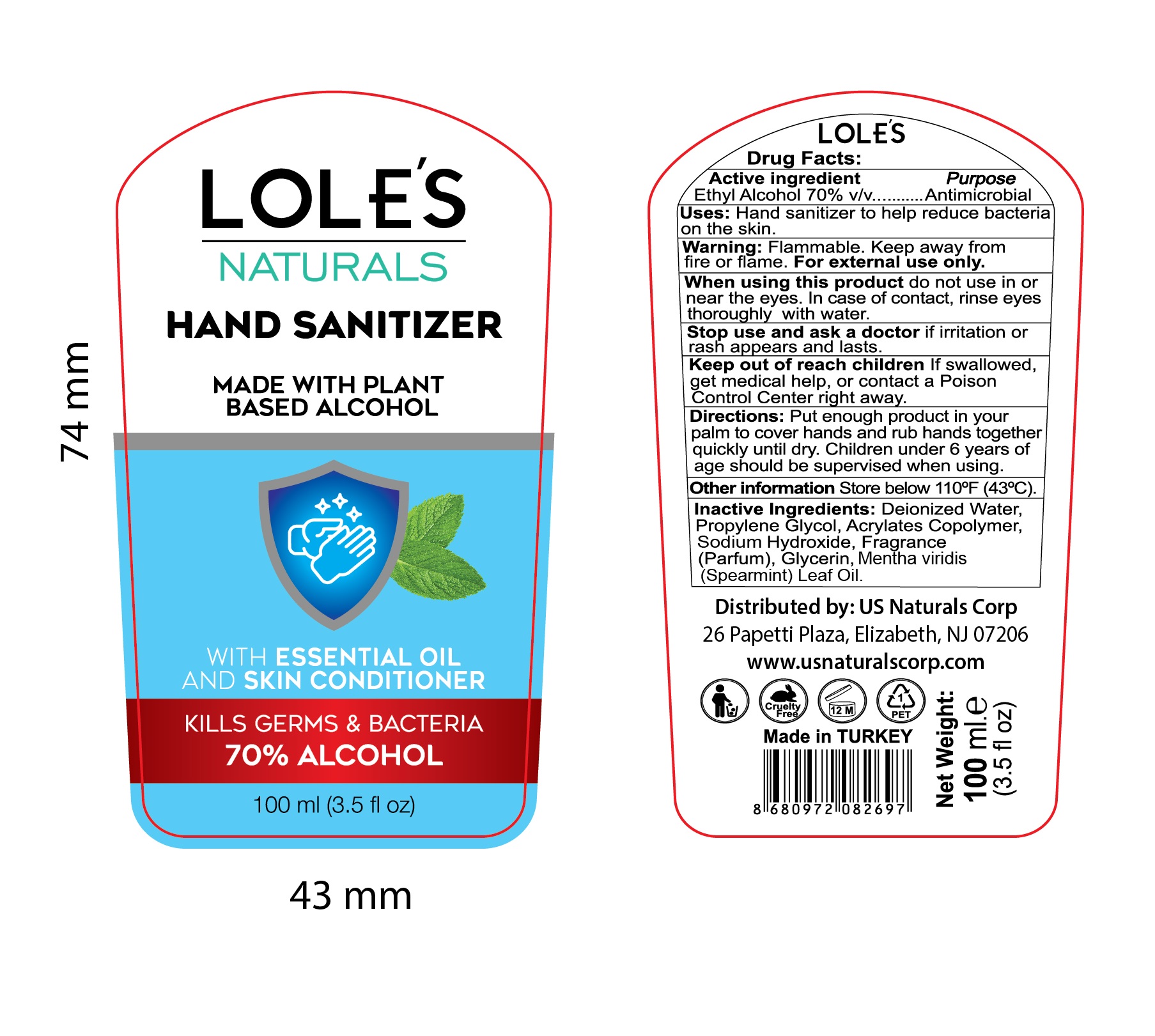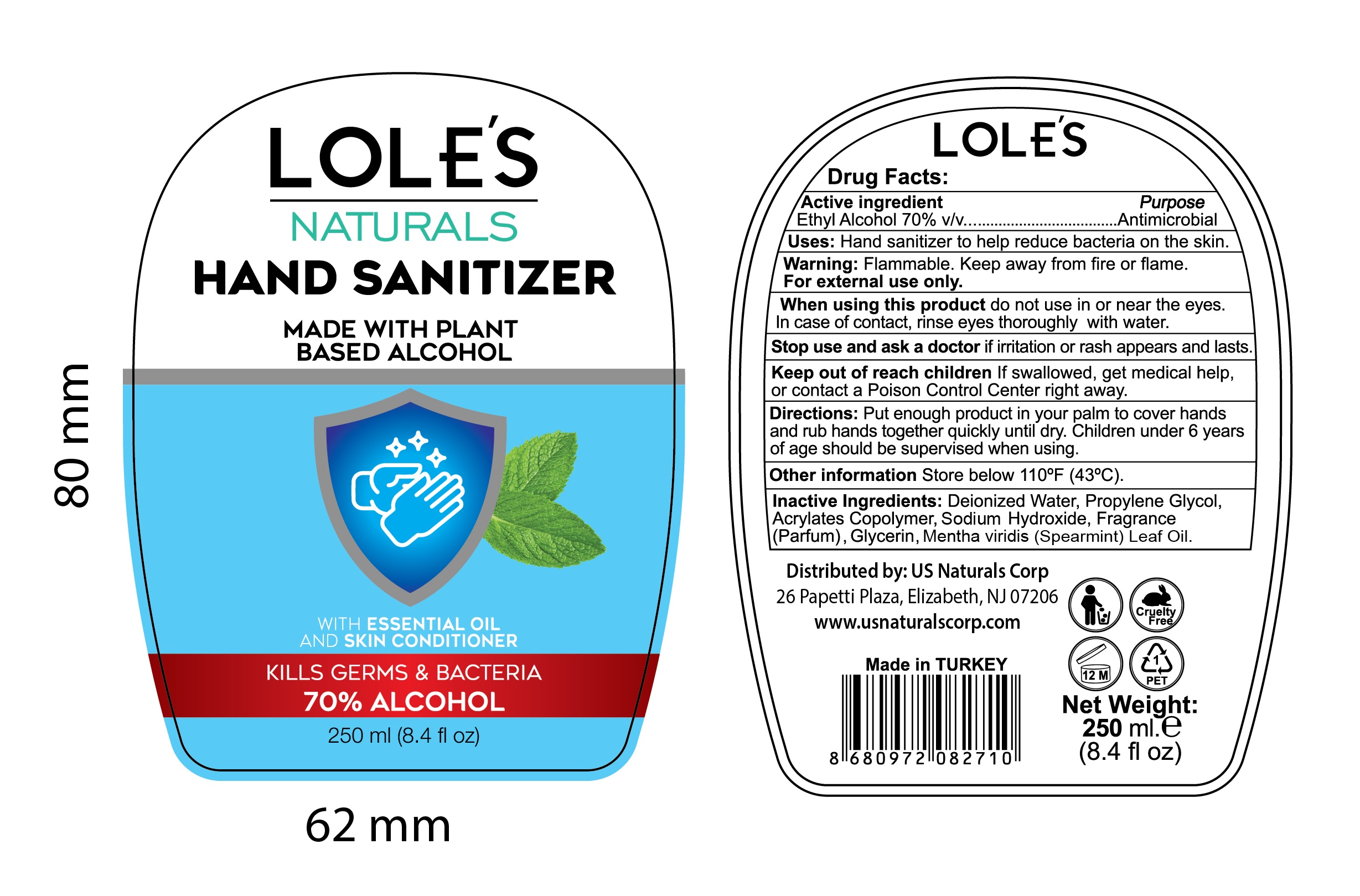 DRUG LABEL: LOLES Naturals Hand Sanitizer
NDC: 73485-001 | Form: GEL
Manufacturer: Diora Kimya Sanayi ve Ticaret Limited Sirketi
Category: otc | Type: HUMAN OTC DRUG LABEL
Date: 20220131

ACTIVE INGREDIENTS: ALCOHOL 70 mL/100 mL
INACTIVE INGREDIENTS: GLYCERIN 1.5 mL/100 mL; SODIUM HYDROXIDE 0.2 mL/100 mL; WATER; BUTYL ACRYLATE/METHYL METHACRYLATE/METHACRYLIC ACID COPOLYMER (18000 MW) 5.75 mL/100 mL; PROPYLENE GLYCOL 1 mL/100 mL

This is a hand sanitizer manufactured according to the Temporary Policy for Preparation of Certain Alcohol-Based Hand Sanitizer Products During the Public Health Emergency (CoViD-19); Guidance for Industry.

The hand sanitizer is manufactured using only the following United States Pharmacopoeia (USP) grade ingredients in the preparation of the product (percentage in final product formulation) consistent with World Health Organization (WHO) recommendations:

1. Alcohol (ethanol) (USP or Food Chemical Codex (FCC) grade) (80%, volume/volume (v/v)) in an aqueous solution denatured according to Alcohol and Tobacco Tax and Trade Bureau regulations in 27 CFR part 20.
2. Glycerol (1.45% v/v).
3. Hydrogen peroxide (0.125% v/v).
4. Sterile distilled water or boiled cold water.

The firm does not add other active or inactive ingredients. Different or additional ingredients may impact the quality and potency of the product.

Active Ingredient(s)

Alcohol 70% v/v. Purpose: Antimicrobial

Purpose

Antimicrobial, Hand Sanitizer

Use

Hand Sanitizer to help reduce bacteria on the skin

Warnings

For external use only. Flammable. Keep away from heat or flame

Do not use

When using this product do not use in ot near the eyes. In case of contact, rinse eyes thoroughly with water.

Stop use and ask a doctor if irritation or rash appears and lasts.

When using this product do not use in ot near the eyes. In case of contact, rinse eyes thoroughly with water.

Stop use and ask a doctor if irritation or rash appears and lasts.

Keep out of reach of children. If swallowed, get medical help or contact a Poison Control Center right away.

Stop use and ask a doctor if irritation or rash occurs. These may be signs of a serious condition.

Keep out of reach of children. If swallowed, get medical help or contact a Poison Control Center right away.

Directions

- Put enough product in your palm to cover hands and rub hands together quickly until dry.
- Children under 6 years of age should be supervised when using.

Other information

- Store below 110 F (43 C)

Inactive ingredients

Deionized Water, Propylene Glycol, Acrylates Copolymer, Sodium Hyroxide, Fragrance (Parfum), Glycerin, Mentha viridis (Spearmint) Leaf Oil

Package Label - Principal Display Panel

100 mL NDC: 73485-001-01

PACKAGE LABEL

250 mL NDC: 73485-001-02